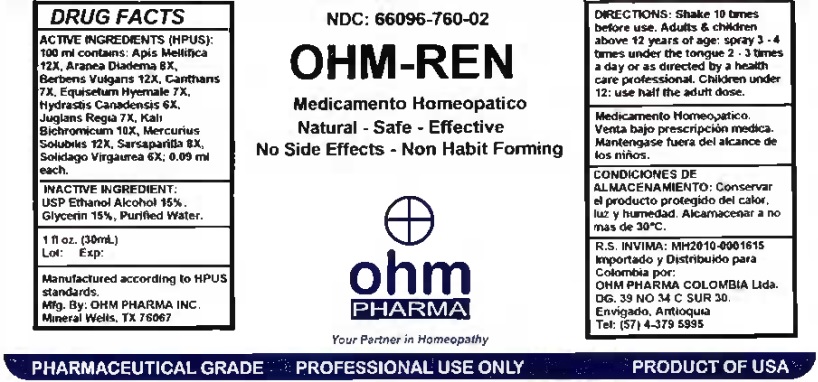 DRUG LABEL: OHM-REN
NDC: 66096-760 | Form: SPRAY
Manufacturer: OHM PHARMA INC.
Category: homeopathic | Type: HUMAN PRESCRIPTION DRUG LABEL
Date: 20260128

ACTIVE INGREDIENTS: APIS MELLIFERA 12 [hp_X]/30 mL; ARANEUS DIADEMATUS 8 [hp_X]/30 mL; BERBERIS VULGARIS ROOT BARK 12 [hp_X]/30 mL; LYTTA VESICATORIA 7 [hp_X]/30 mL; EQUISETUM HYEMALE 7 [hp_X]/30 mL; GOLDENSEAL 6 [hp_X]/30 mL; JUGLANS REGIA LEAF 7 [hp_X]/30 mL; POTASSIUM DICHROMATE 10 [hp_X]/30 mL; MERCURIUS SOLUBILIS 12 [hp_X]/30 mL; SARSAPARILLA 8 [hp_X]/30 mL; SOLIDAGO VIRGAUREA FLOWERING TOP 6 [hp_X]/30 mL
INACTIVE INGREDIENTS: WATER; GLYCERIN; ALCOHOL

OHM-REN

ACTIVE INGREDIENT

ACTIVE INGREDIENTS (HPUS): 100 ml contains: Apis Mellifica 12X, Aranea Diadema 8X, Berberis Vulgaris 12X, Cantharis 7X, Equisetum Hyemale 7X, Hydrastis Canadensis 6X, Juglans Regia 7X, Kali Bichromicum 10X, Mercurius Solubilis 12X, Sarsaparilla 8X, Solidago Virgaurea 6X; 0.09 ml each.

INDICATIONS AND USAGE

USES: Temporarily relieves acute or chronic functional ailments of the kidneys and/or urinary track.**

WARNINGS

Medicamento Homeopatico.

Venta bajo prescripcion medica.

Mantengase fuera del alcance de los niños.

KEEP OUT OF REACH OF CHILDREN

Mantengase fuera del alcance de los niños.

DOSAGE AND ADMINISTRATION

DIRECTIONS: Shake 10 times before use. Adults & children above 12 years of age: spray 3 - 4 times under the tongue 2 - 3 times a day or as directed by a health care professional. Children under 12: use half the adult dose.

OTHER SAFETY INFORMATION

CONDICIONES DE ALMACENAMIENTO: Conservar el producto protegido del calor, luz y humedad. Alcamacenar a no mas de 30°C.

INACTIVE INGREDIENT:

USP Ethanol Alcohol 15%,

Glycerin 15%, Purified Water.

QUESTIONS

R.S. INVIMA: MH2010-0001615

Importado y distribuido para Colombia por
OHM PHARMA COLOMBIA SAS
Vereda El Abra
Sector Saunas Medicas
Finca el Rinconcito
Cota, Cundinamarca, Colombia
Tel: (+57) 320-230-7789

Manufactured according to HPUS

standards.

Mfg. By: OHM PHARMA INC.

Mineral Wells, TX 76067

PACKAGE LABEL

NDC: 66096-760-02

OHM-REN

Medicamento Homeopatico

Natural - Safe - Effective

No Side Effects - Non Habit Forming

PURPOSE

USES: Temporarily relieves acute or chronic functional ailments of the kidneys and/or urinary track.**